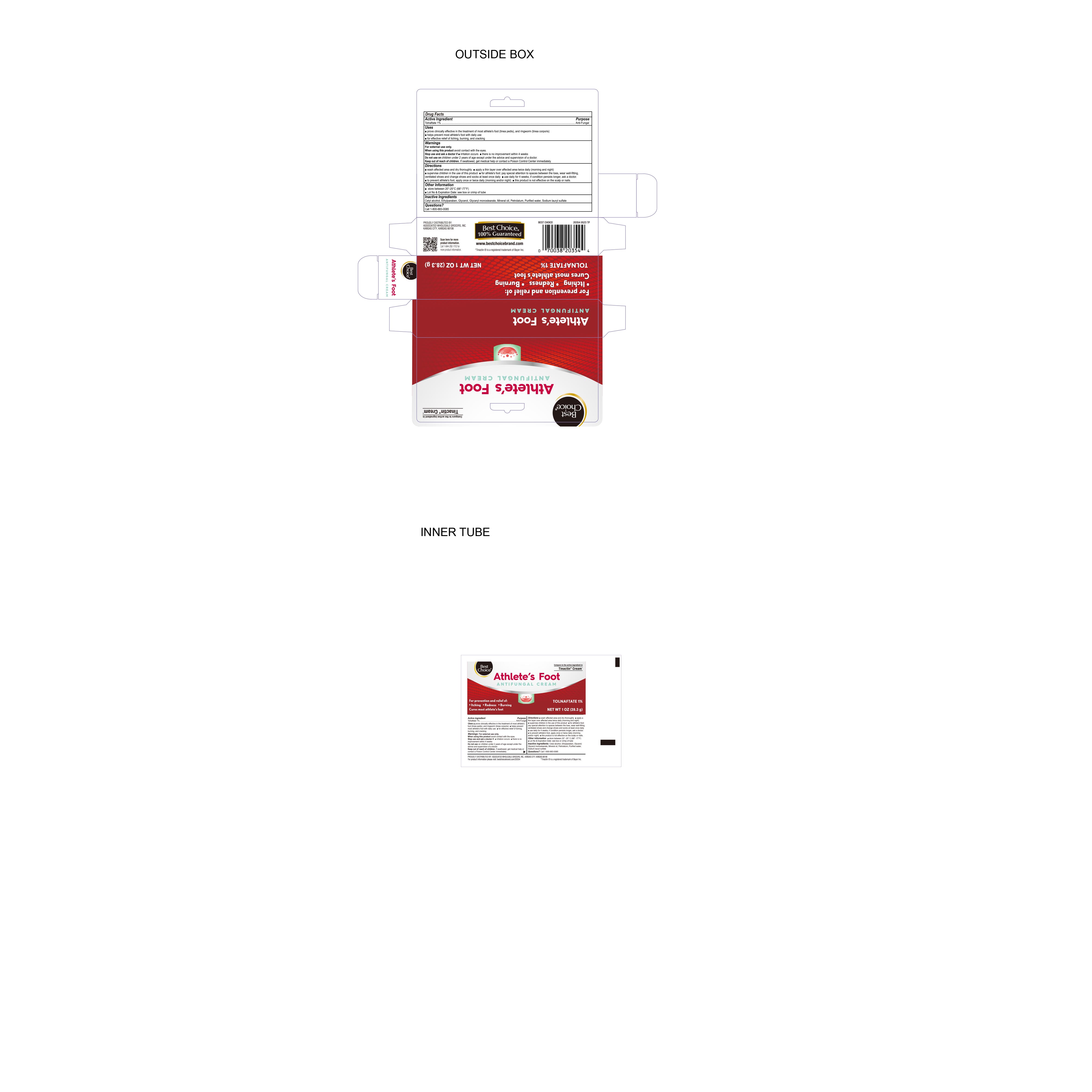 DRUG LABEL: Tolnaftate
NDC: 69396-130 | Form: CREAM
Manufacturer: Trifecta Pharmaceuticals USA, LLC
Category: otc | Type: HUMAN OTC DRUG LABEL
Date: 20241231

ACTIVE INGREDIENTS: TOLNAFTATE 1 g/100 g
INACTIVE INGREDIENTS: ETHYLPARABEN; GLYCERIN; MINERAL OIL; GLYCERYL MONOSTEARATE; PETROLATUM; WATER; SODIUM LAURYL SULFATE; CETYL ALCOHOL

Best Choice Athlete's Foot

Active ingredient

Tolnaftate 1%

Purpose

Anti-Fungal

Uses

● proven clinically effective in the treatment of most athlete's foot (tinea pedis), and ringworm (tinea corporis) ● helps prevent most athlete's foot with daily use ● for effective relief of itching, burning and cracking.

Keep out of reach of children

If swallowed, get medical help or contact a poison control center immediately

Warnings

For external use only.

When using this product avoid contact with the eyes.

Stop use and ask a doctor if● irritation occurs ● there is no improvement within 4 weeks

Do not use on children under 2 years of age except under the advice and supervision of a doctor.

Directions

● wash affected area and dry thoroughly

● apply a thin layer over affected area twice daily (morning and night)

● supervise children in the use of this product

● for athlete’s foot: pay special attention to spaces between the toes, wear well-fitting ventilated shoes and change shoes and socks at least once daily.

● use daily for 4 weeks; if conditions persists longer, ask a doctor.

● to prevent athlete's foot, apply once or twice daily (morning and/or night)

● this product is not effective on the scalp or nails.

Questions

Call 1-800-883-0085

Inactive ingredients

Cetyl alcohol, ethylparaben, glycerol, mineral oil, glycerol monostearate, petrolatum, purified water, sodium lauryl sulfate

Other information

● store between 20° to 25°C (68° to 77°F) ● Lot No & Expiration Date: See box or crimp of tube.

Distrubuted by

Proudly distributed by

Associated Wholesale Grocers Inc

Kansas City, Kansas 66106

Tinactin® is a registered trademark of Bayer Inc.

www.bestchoicebrand.com